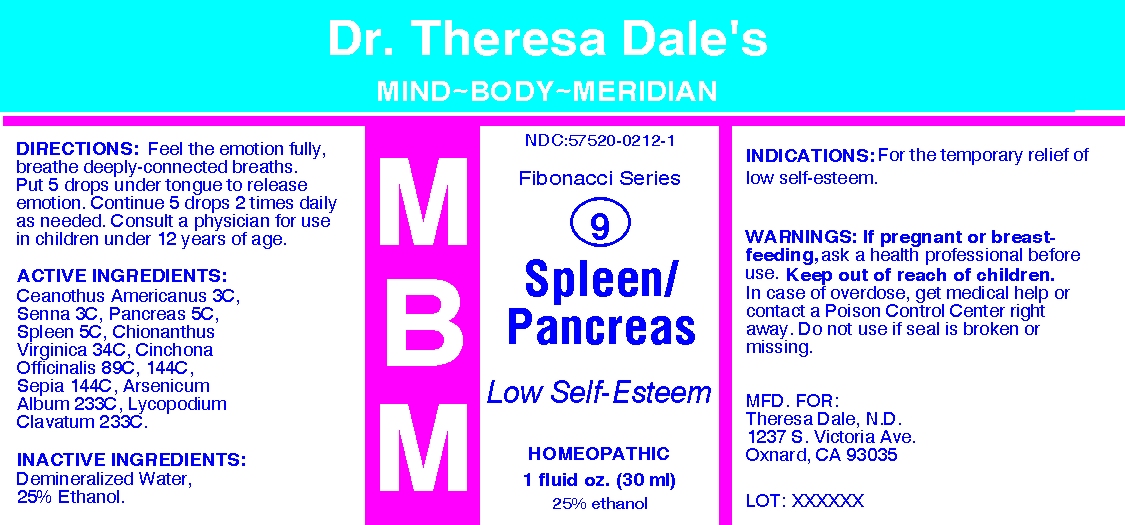 DRUG LABEL: MBM 9 Spleen Pancreas
NDC: 57520-0212 | Form: LIQUID
Manufacturer: Apotheca Company
Category: homeopathic | Type: HUMAN OTC DRUG LABEL
Date: 20100723

ACTIVE INGREDIENTS: CEANOTHUS AMERICANUS LEAF 3 [hp_C]/1 mL; SENNA LEAF 3 [hp_C]/1 mL; SUS SCROFA PANCREAS 5 [hp_C]/1 mL; SUS SCROFA SPLEEN 5 [hp_C]/1 mL; CHIONANTHUS VIRGINICUS BARK 34 [hp_C]/1 mL; CINCHONA OFFICINALIS BARK 144 [hp_C]/1 mL; SEPIA OFFICINALIS JUICE 144 [hp_C]/1 mL; ARSENIC TRIOXIDE 233 [hp_C]/1 mL; LYCOPODIUM CLAVATUM SPORE 233 [hp_C]/1 mL
INACTIVE INGREDIENTS: WATER; ALCOHOL

MBM 9 Spleen Pancreas

ACTIVE INGREDIENT

ACTIVE INGREDIENTS: Ceanothus americanus 3C, Senna 3C, Pancreas 5C, Spleen 5C, Chionanthus virginica 34C, Cinchona officinalis 89C, 144C, Sepia 144C, Arsenicum albun 233C, Lycopodium clavatum 233C.

PURPOSE

INDICATIONS: For the temporary relief of low self-esteem.

WARNINGS

WARNINGS: If pregnant or breast-feeding, ask a health professional before use. Keep out of reach of children. In case of overdose, get medical help or contact a Poison Control Center right away. Do not use if seal is broken or missing.

DOSAGE AND ADMINISTRATION

DIRECTIONS: Feel the emotion fully, breathe deeply-connected breaths. Put 5 drops under tongue to release emotion. Continue 5 drops 2 times daily as needed. Consult a physician for use in children under 12 years of age.

INACTIVE INGREDIENTS: Demineralized water, 25% Ethanol

QUESTIONS

MFD. FOR:

Theresa Dale, N. D.

1237 S Victoria Ave.

Oxnard, CA 93035

PACKAGE LABEL

Dr. Theresa Dale's

Mind-Body-Meridian

Fibonacci Series

9

SPLEEN/PANCREAS

Low Self-Esteem

HOMEOPATHIC

1 FL OZ (30 ML)